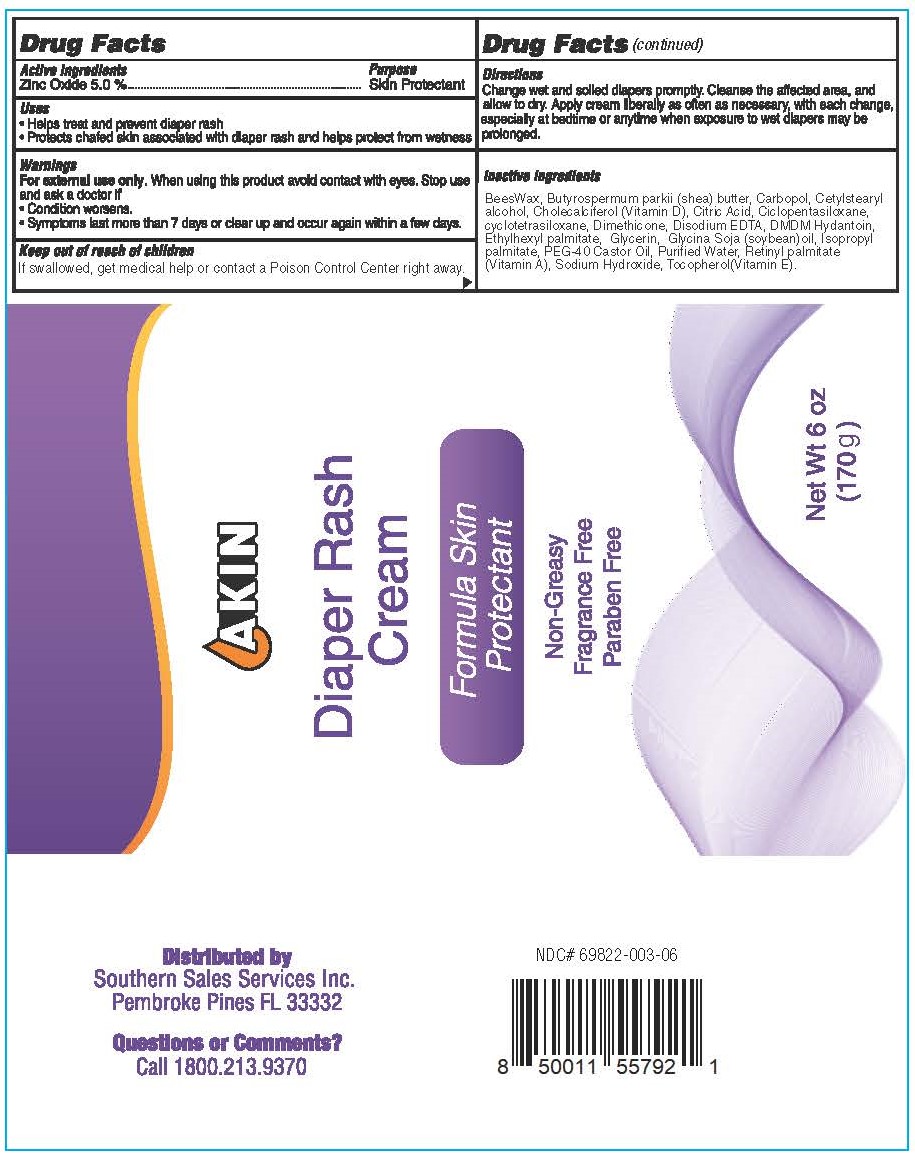 DRUG LABEL: Akin Diaper Rash
NDC: 69822-003 | Form: CREAM
Manufacturer: Southern Sales & Service, Inc.
Category: otc | Type: HUMAN OTC DRUG LABEL
Date: 20231129

ACTIVE INGREDIENTS: ZINC OXIDE 50 mg/1 g
INACTIVE INGREDIENTS: YELLOW WAX; SHEA BUTTER; CARBOMER HOMOPOLYMER, UNSPECIFIED TYPE; CETOSTEARYL ALCOHOL; CHOLECALCIFEROL; CITRIC ACID ACETATE; CYCLOMETHICONE 4; CYCLOMETHICONE 5; DIMETHICONE; EDETATE DISODIUM ANHYDROUS; DMDM HYDANTOIN; ETHYLHEXYL PALMITATE; GLYCERIN; SOYBEAN OIL; ISOPROPYL PALMITATE; PEG-40 CASTOR OIL; WATER; VITAMIN A PALMITATE; SODIUM HYDROXIDE; TOCOPHEROL

Akin Diaper Rash

Active ingredients

Zinc Oxide 5.0%

Purpose

Skin Protectant

Uses

- Helps treat and prevent diaper rash
- Protects chafed skin associated with diaper rash and helps protect from wetness

Warnings

When using this product avoid contact with eyes. For external use only.

Stop use and ask a doctor if

- Condition worsens.
- Symptoms last more than 7 days or clear up and occur again within a few days.

Keep out of reach of children

If swallowed, get medical help or contact a Poison Control Center right away.

Directions

Change wet and soiled diapers promptly. Cleanse the affected area, and allow to dry. Apply cream liberally as often as necessary, with each change, especially at bedtime or anytime when exposure to wet diapers may be prolonged.

Inactive ingredients

BeesWax, Butyrospermum parkii (shea) butter, Carbopol, Cetylstearyl alcohol, Cholecalciferol (Vitamin D), Citric Acid, Ciclopentasiloxane, cyclotetrasiloxane, Dimethicone, Disodium EDTA, DMDM Hydantoin, Ethylhexyl palmitate, Glycerin, Glycina Soja (soybean)oil, Isopropyl palmitate, PEG-40 Castor Oil, Purified Water, Retinyl palmitate (Vitamin A), Sodium Hydroxide, Tocopherol(Vitamin E).